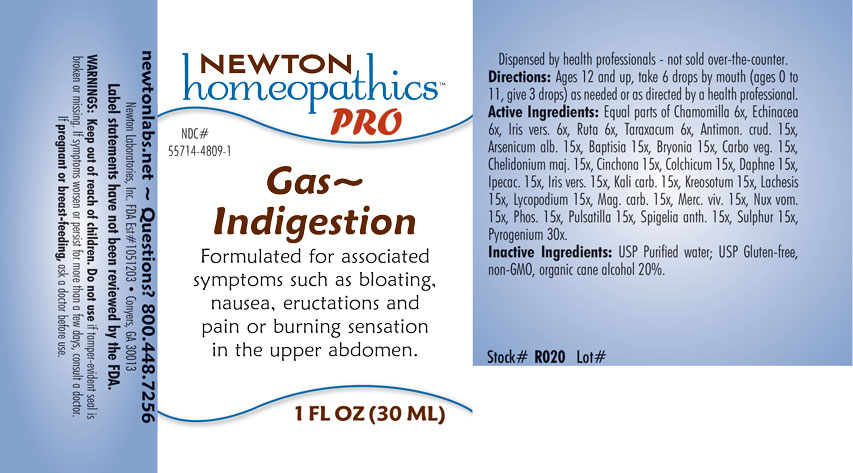 DRUG LABEL: Gas-Indigestion
NDC: 55714-4809 | Form: LIQUID
Manufacturer: Newton Laboratories, Inc.
Category: homeopathic | Type: HUMAN OTC DRUG LABEL
Date: 20250210

ACTIVE INGREDIENTS: MERCURY 15 [hp_X]/1 mL; STRYCHNOS NUX-VOMICA SEED 15 [hp_X]/1 mL; MATRICARIA CHAMOMILLA 6 [hp_X]/1 mL; MAGNESIUM CARBONATE 15 [hp_X]/1 mL; RUTA GRAVEOLENS FLOWERING TOP 6 [hp_X]/1 mL; BAPTISIA TINCTORIA ROOT 15 [hp_X]/1 mL; TARAXACUM OFFICINALE 6 [hp_X]/1 mL; ANTIMONY TRISULFIDE 15 [hp_X]/1 mL; ARSENIC TRIOXIDE 15 [hp_X]/1 mL; BRYONIA ALBA ROOT 15 [hp_X]/1 mL; ACTIVATED CHARCOAL 15 [hp_X]/1 mL; CHELIDONIUM MAJUS 15 [hp_X]/1 mL; CINCHONA OFFICINALIS BARK 15 [hp_X]/1 mL; COLCHICUM AUTUMNALE BULB 15 [hp_X]/1 mL; DAPHNE ODORA BARK 15 [hp_X]/1 mL; IPECAC 15 [hp_X]/1 mL; IRIS VERSICOLOR ROOT 15 [hp_X]/1 mL; POTASSIUM CARBONATE 15 [hp_X]/1 mL; WOOD CREOSOTE 15 [hp_X]/1 mL; LACHESIS MUTA VENOM 15 [hp_X]/1 mL; LYCOPODIUM CLAVATUM SPORE 15 [hp_X]/1 mL; ECHINACEA, UNSPECIFIED 6 [hp_X]/1 mL; RANCID BEEF 30 [hp_X]/1 mL; PHOSPHORUS 15 [hp_X]/1 mL; ANEMONE PULSATILLA 15 [hp_X]/1 mL; SPIGELIA ANTHELMIA 15 [hp_X]/1 mL; SULFUR 15 [hp_X]/1 mL
INACTIVE INGREDIENTS: WATER; ALCOHOL

Gas 4809L

INDICATIONS & USAGE SECTION

Formulated for associated symptoms such as bloating, nausea, eructations and pain or burning sensation in the upper abdomen.

DOSAGE & ADMINISTRATION SECTION

Directions: Ages 12 and up, take 6 drops by mouth (ages 0 to 11, give 3 drops) as needed or as directed by a health professional.

OTC - ACTIVE INGREDIENT SECTION

Equal parts of Chamomilla 6x, Echinacea 6x, Iris versicolor 6x, Ruta graveolens 6x, Taraxacum officinale 6x, Antimonium crudum 15x, Arsenicum album 15x, Baptisia tinctoria 15x, Bryonia 15x, Carbo vegetabilis 15x, Chelidonium majus 15x, Cinchona officinalis 15x, Colchicum autumnale 15x, Daphne indica 15x, Ipecacuanha 15x, Iris versicolor 15x, Kali carbonicum 15x, Kreosotum 15x, Lachesis mutus 15x, Lycopodium clavatum 15x, Magnesia carbonica 15x, Mercurius vivus 15x, Nux vomica 15x, Phosphorus 15x, Pulsatilla 15x, Spigelia anthelmia 15x, Sulphur 15x, Pyrogenium 30x.

OTC - PURPOSE SECTION

Formulated for associated symptoms such as bloating, nausea, eructations and pain or burning sensation in the upper abdomen

INACTIVE INGREDIENT SECTION

Inactive Ingredients: USP Purified Water; USP Gluten-free, non-GMO, organic cane alcohol 20%.

QUESTIONS SECTION

newtonlabs.net - Questions? 800.448.7256

Newton Laboratories, Inc. FDA Est # 1051203 Conyers, GA 30013

WARNINGS SECTION

WARNINGS: Keep out of reach of children. Do not use if tamper-evident seal is broken or missing. If symptoms worsen or persist for more than a few days, consult a doctor. If pregnant or breast-feeding, ask a doctor before use.

OTC - PREGNANCY OR BREAST FEEDING SECTION

If pregnant or breast-feeding, ask a doctor before use.

OTC - KEEP OUT OF REACH OF CHILDREN SECTION

Keep out of reach of children.